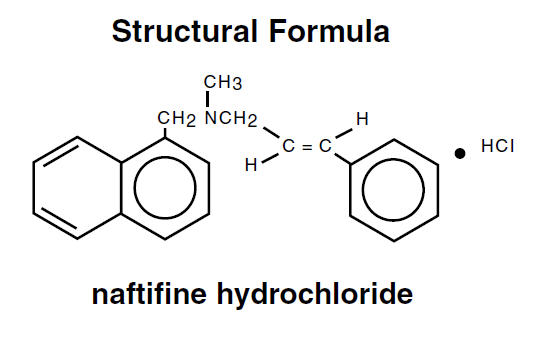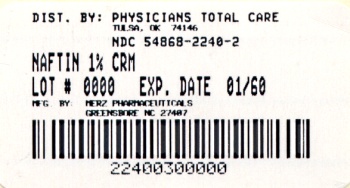 DRUG LABEL: Naftin
NDC: 54868-2240 | Form: CREAM
Manufacturer: Physicians Total Care, Inc.
Category: prescription | Type: HUMAN PRESCRIPTION DRUG LABEL
Date: 20091222

ACTIVE INGREDIENTS: NAFTIFINE HYDROCHLORIDE 10 mg/1 g
INACTIVE INGREDIENTS: BENZYL ALCOHOL; CETYL ALCOHOL; ISOPROPYL MYRISTATE; POLYSORBATE 60; SORBITAN MONOSTEARATE; STEARYL ALCOHOL

NAFTIN®
NAFTIFINE HCl 1% CREAM

Rx Only

DESCRIPTION

Naftin® Cream, 1% contains the synthetic, broad-spectrum, antifungal agent naftifine hydrochloride. Naftin® Cream, 1% is for topical use only.

Chemical Name

(E)-N-Cinnamyl-N-methyl-1-naphthalenemethylamine hydrochloride. Naftifine hydrochloride has an empirical formula of C21H21N•HCl and a molecular weight of 323.86.

Active Ingredient
Naftifine hydrochloride | 1%

Inactive Ingredients
benzyl alcohol, cetyl alcohol, cetyl esters wax, isopropyl myristate, polysorbate 60, purified water, sodium hydroxide, sorbitan monostearate, and stearyl alcohol. Hydrochloric acid may be added to adjust pH.

CLINICAL PHARMACOLOGY

Naftifine hydrochloride is a synthetic allylamine derivative. The following in vitro data are available, but their clinical significance is unknown. Naftifine hydrochloride has been shown to exhibit fungicidal activity in vitro against a broad spectrum of organisms, including Trichophyton rubrum, Trichophyton mentagrophytes, Trichophyton tonsurans, Epidermophyton floccosum, Microsporum canis, Microsporum audouini, and Microsporum gypseum; and fungistatic activity against Candida species, including Candida albicans. Naftin® Cream, 1% has only been shown to be clinically effective against the disease entities listed in the INDICATIONS AND USAGE section.

Although the exact mechanism of action against fungi is not known, naftifine hydrochloride appears to interfere with sterol biosynthesis by inhibiting the enzyme squalene 2, 3-epoxidase. This inhibition of enzyme activity results in decreased amounts of sterols, especially ergosterol, and a corresponding accumulation of squalene in the cells.

Pharmacokinetics

In vitro and in vivo bioavailability studies have demonstrated that naftifine penetrates the stratum corneum in sufficient concentration to inhibit the growth of dermatophytes.

Following a single topical application of 1% naftifine cream to the skin of healthy subjects, systemic absorption of naftifine was approximately 6% of the applied dose. Naftifine and/or its metabolites are excreted via the urine and feces with a half-life of approximately two to three days.

INDICATIONS AND USAGE

Naftin® Cream, 1% is indicated for the topical treatment of tinea pedis, tinea cruris and tinea corporis caused by the organisms Trichophyton rubrum, Trichophyton mentagrophytes, and Epidermophyton floccosum.

CONTRAINDICATIONS

Naftin® Cream, 1% is contraindicated in individuals who have shown hypersensitivity to any of its components.

WARNINGS

Naftin® Cream, 1% is for topical use only and not for ophthalmic use.

PRECAUTIONS

General

Naftin® Cream, 1% is for external use only. If irritation or sensitivity develops with the use of Naftin® Cream, 1%, treatment should be discontinued and appropriate therapy instituted. Diagnosis of the disease should be confirmed either by direct microscopic examination of a mounting of infected tissue in a solution of potassium hydroxide or by culture on an appropriate medium.

Information for patients

The patient should be told to:

1. Avoid the use of occlusive dressings or wrappings unless otherwise directed by the physician.
2. Keep Naftin® Cream, 1% away from the eyes, nose, mouth and other mucous membranes.

Carcinogenesis, mutagenesis, impairment of fertility

Long-term animal studies to evaluate the carcinogenic potential of Naftin® Cream, 1% have not been performed. In vitro and animal studies have not demonstrated any mutagenic effect or effect on fertility.

Pregnancy

Teratogenic Effects

Pregnancy Category B

Reproduction studies have been performed in rats and rabbits (via oral administration) at doses 150 times or more the topical human dose and have revealed no evidence of impaired fertility or harm to the fetus due to naftifine. There are, however, no adequate and well controlled studies in pregnant women. Because animal reproduction studies are not always predictive of human response, this drug should be used during pregnancy only if clearly needed.

Nursing mothers

It is not known whether this drug is excreted in human milk. Because many drugs are excreted in human milk, caution should be exercised when Naftin® Cream, 1% is administered to a nursing woman.

Pediatric use

Safety and effectiveness in pediatric patients have not been established.

ADVERSE REACTIONS

During clinical trials with Naftin® Cream, 1%, the incidence of adverse reactions was as follows: burning/stinging (6%), dryness (3%), erythema (2%), itching (2%), local irritation (2%).

DOSAGE AND ADMINISTRATION

A sufficient quantity of Naftin® Cream, 1% should be gently massaged into the affected and surrounding skin areas once a day. The hands should be washed after application. If no clinical improvement is seen after four weeks of treatment with Naftin® Cream, 1%, the patient should be re-evaluated.

HOW SUPPLIED

Naftin® (naftifine hydrochloride) 1% Cream is supplied in the following sizes:

30g—NDC 54868-2240-2 (tube)

STORAGE AND HANDLING

Tubes: Store below 30° (86°F).
Pumps: Store at controlled room temperature: 25°C (77°F);
excursions permitted between 15 - 30°C (59 - 86°F).

Manufactured for: Merz Pharmaceuticals, Greensboro, NC 27140

5011316

©2008 Merz Pharmaceuticals

Rev. 5/08 Printed in U.S.A.

Relabeling of "Additional Barcode" by:
Physicians Total Care, Inc.
Tulsa, OK 74146

PRINCIPAL DISPLAY PANEL - 30g (tube) Carton

NAFTIN®
30g cream

NAFTIFINE HCl 1% CREAM

Rx Only